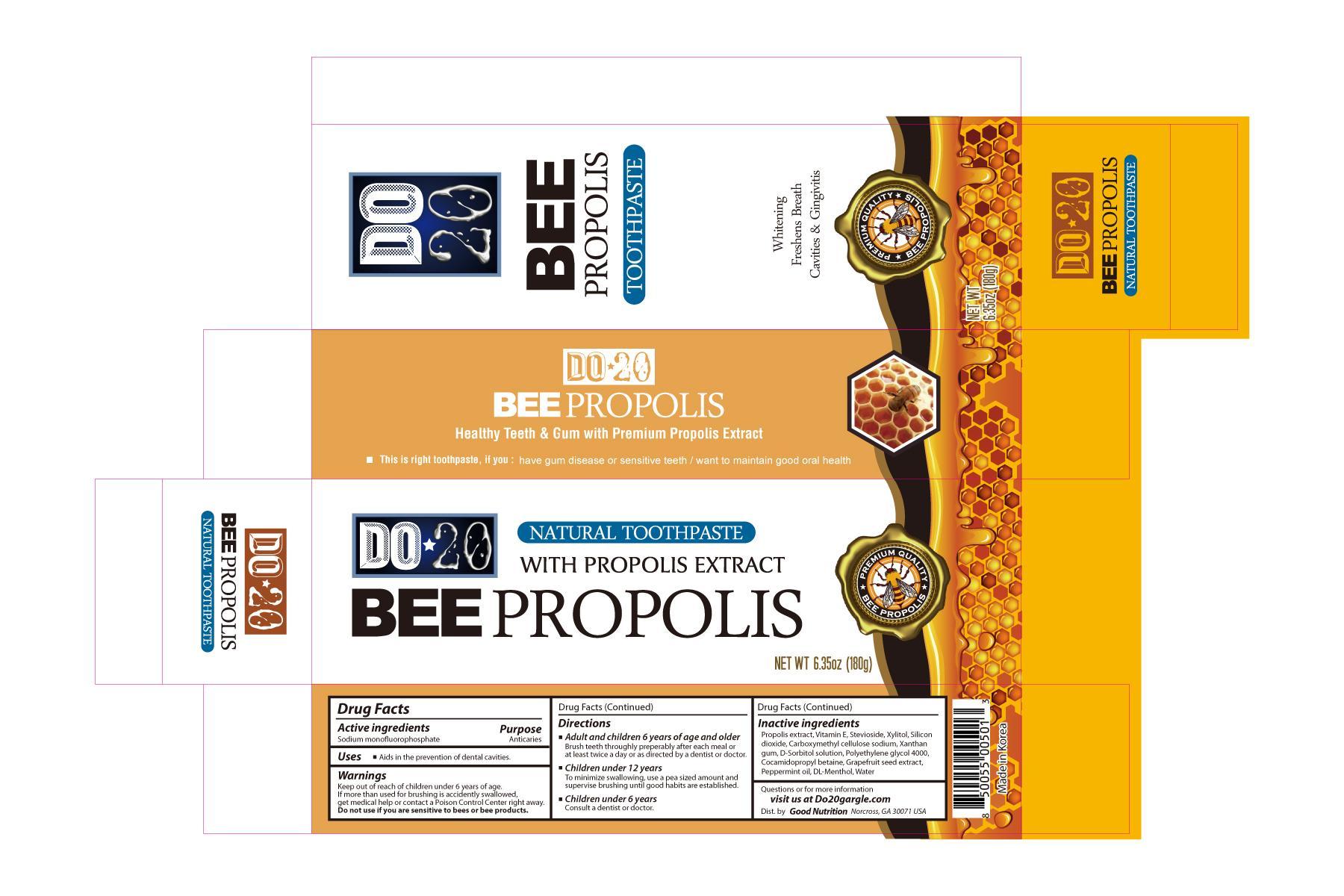 DRUG LABEL: BEEPROPOLIS
NDC: 58964-101 | Form: PASTE, DENTIFRICE
Manufacturer: Sinhwa Life Health Co Ltd
Category: otc | Type: HUMAN OTC DRUG LABEL
Date: 20130714

ACTIVE INGREDIENTS: SODIUM MONOFLUOROPHOSPHATE 100 mg/100 g
INACTIVE INGREDIENTS: PROPOLIS WAX; .ALPHA.-TOCOPHEROL; STEVIOSIDE; XYLITOL; SILICON DIOXIDE; CARBOXYMETHYLCELLULOSE SODIUM; XANTHAN GUM; SORBITOL; POLYETHYLENE GLYCOL 4000; COCAMIDOPROPYL BETAINE; CITRUS PARADISI SEED; PEPPERMINT OIL; RACEMENTHOL; WATER

Drug Facts

Inactive Ingredients

Propolis extract, Vitamin E, Stevioside, Xylitol, Silicon Dioxide,

Carboxymethylcellulose sodium, Xanthan Gum, D-Sorbitol solution,

Polyethylene glycol 4000, Cocamidopropyl betaine, Grapefruit seed extract,

Peppermint Oil, DL-Menthol, Water

Active Ingredients

Sodium monofluorophosphate

Purpose

Anticaries

Keep out of reach of children under 6 years of age.

INDICATIONS AND USAGE

Uses - Aids in the prevention of cavities

Directions

Adults and children 6 years of age and older - Brush teeth thoroughly preferably after each meal or at least twice a day

or as directed by a dentist or doctor

Children under 12 years of age - To minimize swallowing, use a pea sized amount and supervise brushing

until good habits are established

Children under 5 years of age - Consult a dentist or doctor

Warnings

Keep out of reach of children under 6 years of age.

If more than used for brushing is accidentally swallowed, get medical help

or contact a Poison Control Center right away.

Do not Use if you are sensitive to bees or bee products.